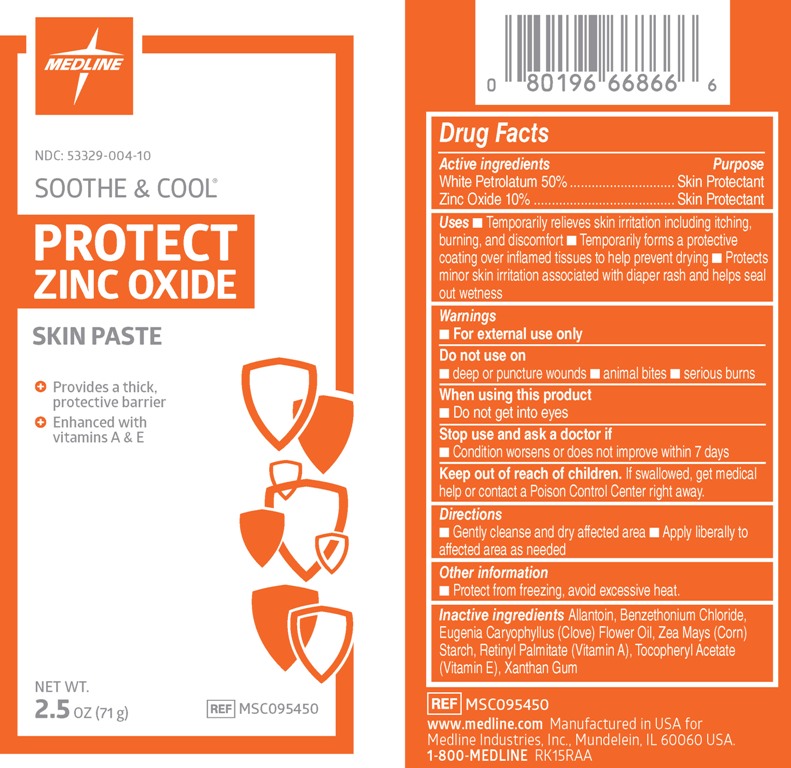 DRUG LABEL: Soothe and Cool Protect
NDC: 53329-004 | Form: PASTE
Manufacturer: Medline Industries, Inc.
Category: otc | Type: HUMAN OTC DRUG LABEL
Date: 20190111

ACTIVE INGREDIENTS: ZINC OXIDE 100 mg/1 g; PETROLATUM 500 mg/1 g
INACTIVE INGREDIENTS: ALLANTOIN; BENZETHONIUM CHLORIDE; CHOLECALCIFEROL; CLOVE OIL; VITAMIN A PALMITATE; ALPHA-TOCOPHEROL ACETATE; STARCH, CORN; XANTHAN GUM

Drug Facts

Active ingredients

White Petrolatum 50%

Zinc Oxide 10%

Purpose

Skin Protectant

Uses

■ Temporarily relieves skin irritation including itching, burning, and discomfort

■ Temporarily forms a protective coating over inflamed tissues to help prevent drying

■ Protects minor skin irritation associated with diaper rash and helps seal out wetness

Warnings

For external use only

Do not use on

- deep or puncture wounds
- animal bites
- serious burns

When using this product

- Do not get into the eyes

Stop use and ask a doctor if

- Condition worsens or does not improve within 7 days

Keep out of reach of children

If swallowed, get medical help or contact a Poison Control Center right away.

Directions

- gently cleanse and dry affected area
- apply liberally to affected area as needed

Other information

Protect from freezing, avoid excessive heat.

Inactive ingredients

Allantoin, Benzethonium Chloride, Eugenia Caryophyllus (Clove) Flower Oil, Zea Mays (Corn) Starch, Retinyl Palmitate (Vitamin A), Tocopheryl Acetate (Vitamin E), Xanthan Gum

www.medline.com

Manufactured in USA for Medline Industries, Inc.,

Mundelein, IL 60060 USA.
1-800-MEDLINE

PACKAGE LABEL

NDC: 53329-004-10

SOOTHE & COOL®

PROTECT

ZINC OXIDE

SKIN PASTE

- Provides a thick, protective barrier
- Enhanced with vitamins A & E

Net Wt. 2.5 oz (71 g)

REF MSC095450